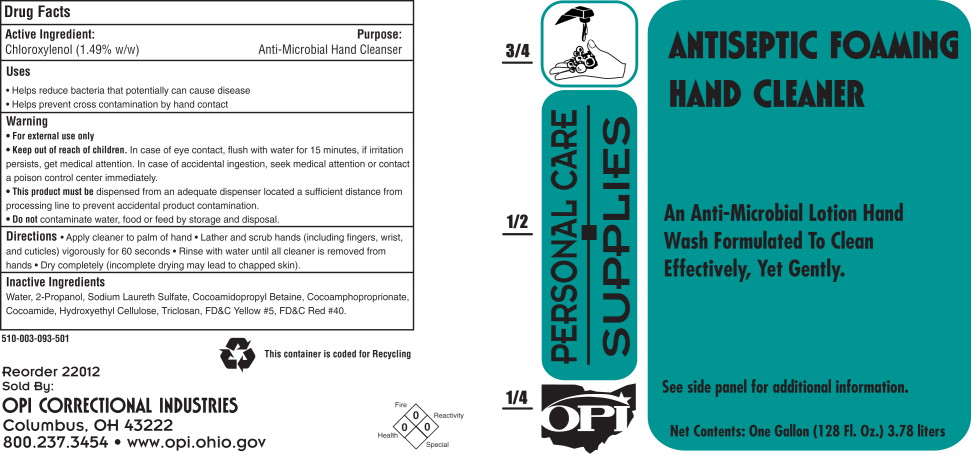 DRUG LABEL: OPI Antiseptic Foaming Hand Cleaner
NDC: 43196-510 | Form: LIQUID
Manufacturer: OPI Correctional Industries
Category: otc | Type: HUMAN OTC DRUG LABEL
Date: 20110307

ACTIVE INGREDIENTS: chloroxylenol 15.75 g/1000 mL
INACTIVE INGREDIENTS: water; sodium laureth sulfate; cocamidopropyl betaine; hydroxyethyl cellulose (2000 CPS at 1%); isopropyl alcohol; coco diethanolamide; triclosan

OPI Antiseptic Foaming Hand Cleaner

Drug Facts

Active Ingredient:

Chloroxylenol (1.49% w/w)

Purpose:

Anti-Microbial Hand Cleanser

Uses

- Helps reduce bacteria that potentially can cause disease
- Helps prevent cross contamination by hand contact

Warnings

- For external use only

- Keep out of reach of children.
- In case of eye contact flush with water for 15 minutes, if irritation persists, get medical attention.
- In case of accidental ingestion, seek medical attention or contact a poison control center immediately.
- This product must be dispensed from an adequate dispenser located a sufficient distance from processing line to prevent accidental product contamination.
- Do not contaminate water, food or feed by storage and disposal.

Directions

- Apply cleaner to palm of hand
- Lather and scrub hands (including fingers, wrist, and cuticles) vigorously for 60 seconds
- Rinse with water until all cleaner is removed from hands
- Dry completely (incomplete drying may lead to chapped skin).

Inactive Ingredients

Water, 2-Propanol, Sodium Laureth Sulfate, Cocoamidopropyl Betaine, Cocoamphoproprionate,

Cocoamide, Hydroxyethyl Cellulose, Triclosan

Principal Display Panel

Bottle Label:

OPI

PERSONAL CARE SUPPLIES

ANTISEPTIC FOAMING HAND CLEANER

An Anti-Microbial Lotion Hand

Wash Formulated To Clean

Effectively, Yet Gently.

See side panel for additional information.